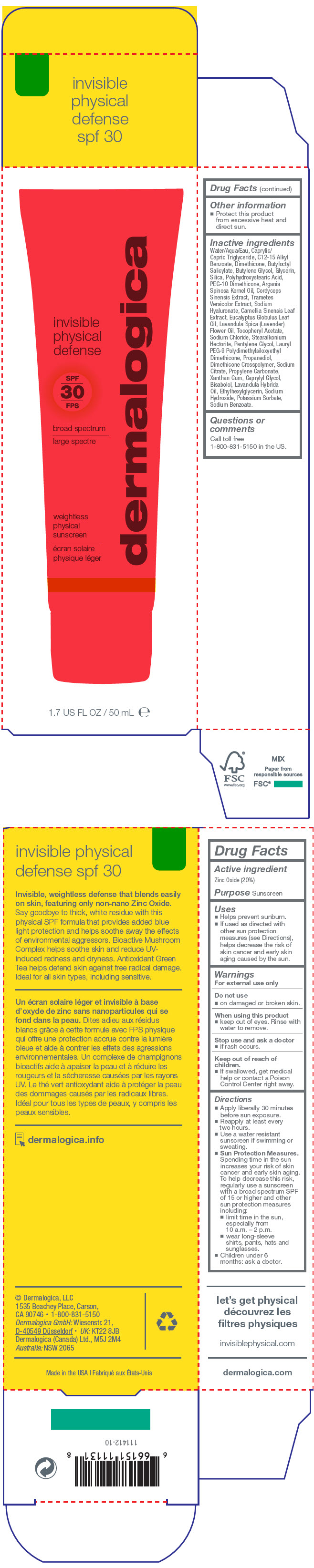 DRUG LABEL: Invisible Physical Defense SPF 30
NDC: 68479-909 | Form: LOTION
Manufacturer: Dermalogica, Inc.
Category: otc | Type: HUMAN OTC DRUG LABEL
Date: 20200305

ACTIVE INGREDIENTS: Zinc Oxide 200 mg/1 mL
INACTIVE INGREDIENTS: Water; MEDIUM-CHAIN TRIGLYCERIDES; ALKYL (C12-15) BENZOATE; Dimethicone; Butyloctyl Salicylate; Glycerin; Butylene Glycol; SILICON DIOXIDE; POLYHYDROXYSTEARIC ACID STEARATE; PEG-10 DIMETHICONE (600 CST); ARGAN OIL; OPHIOCORDYCEPS SINENSIS; TRAMETES VERSICOLOR FRUITING BODY; HYALURONATE SODIUM; EUCALYPTUS OIL; GREEN TEA LEAF; .ALPHA.-TOCOPHEROL ACETATE; LAVENDER OIL; Sodium Chloride; Stearalkonium Hectorite; Pentylene Glycol; Lauryl PEG-9 Polydimethylsiloxyethyl Dimethicone; Propanediol; DIMETHICONE CROSSPOLYMER (450000 MPA.S AT 12% IN CYCLOPENTASILOXANE); SODIUM CITRATE, UNSPECIFIED FORM; Propylene Carbonate; Xanthan Gum; Caprylyl Glycol; LEVOMENOL; Ethylhexylglycerin; LAVANDIN OIL; Sodium Hydroxide; Potassium Sorbate; Sodium Benzoate

Invisible Physical Defense SPF 30

Drug Facts

Active ingredient

Zinc Oxide (20%)

Purpose

Sunscreen

Uses

- Helps prevent sunburn.
- If used as directed with other sun protection measures (see Directions), helps decrease the risk of skin cancer and early skin aging caused by the sun.

Warnings

For external use only

Do not use

- on damaged or broken skin.

When using this product

- keep out of eyes. Rinse with water to remove.

Stop use and ask a doctor

- if rash occurs.

Keep out of reach of children.

- If swallowed, get medical help or contact a Poison Control Center right away.

Directions

- Apply liberally 30 minutes before sun exposure.
- Reapply at least every two hours.
- Use a water resistant sunscreen if swimming or sweating.
- Sun Protection Measures. Spending time in the sun increases your risk of skin cancer and early skin aging. To help decrease this risk, regularly use a sunscreen with a broad spectrum SPF of 15 or higher and other sun protection measures including:
  - limit time in the sun, especially from 10 a.m. – 2 p.m.
  - wear long-sleeve shirts, pants, hats and sunglasses.
- Children under 6 months: ask a doctor.

Other information

- Protect this product from excessive heat and direct sun.

Inactive ingredients

Water/Aqua/Eau, Caprylic/Capric Triglyceride, C12-15 Alkyl Benzoate, Dimethicone, Butyloctyl Salicylate, Butylene Glycol, Glycerin, Silica, Polyhydroxystearic Acid, PEG-10 Dimethicone, Argania Spinosa Kernel Oil, Cordyceps Sinensis Extract, Trametes Versicolor Extract, Sodium Hyaluronate, Camellia Sinensis Leaf Extract, Eucalyptus Globulus Leaf Oil, Lavandula Spica (Lavender) Flower Oil, Tocopheryl Acetate, Sodium Chloride, Stearalkonium Hectorite, Pentylene Glycol, Lauryl PEG-9 Polydimethylsiloxyethyl Dimethicone, Propanediol, Dimethicone Crosspolymer, Sodium Citrate, Propylene Carbonate, Xanthan Gum, Caprylyl Glycol, Bisabolol, Lavandula Hybrida Oil, Ethylhexylglycerin, Sodium Hydroxide, Potassium Sorbate, Sodium Benzoate.

Questions or comments

Call toll free 1-800-831-5150 in the US.

PRINCIPAL DISPLAY PANEL - 50 mL Tube Carton

invisible
physical
defense

dermalogica

SPF
30

broad spectrum

weightless
physical
sunscreen

1.7 US FL OZ / 50 mL ℮